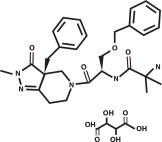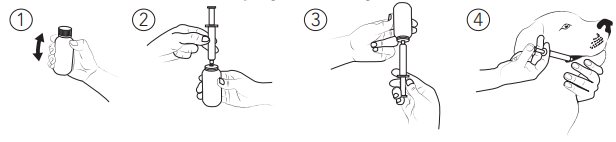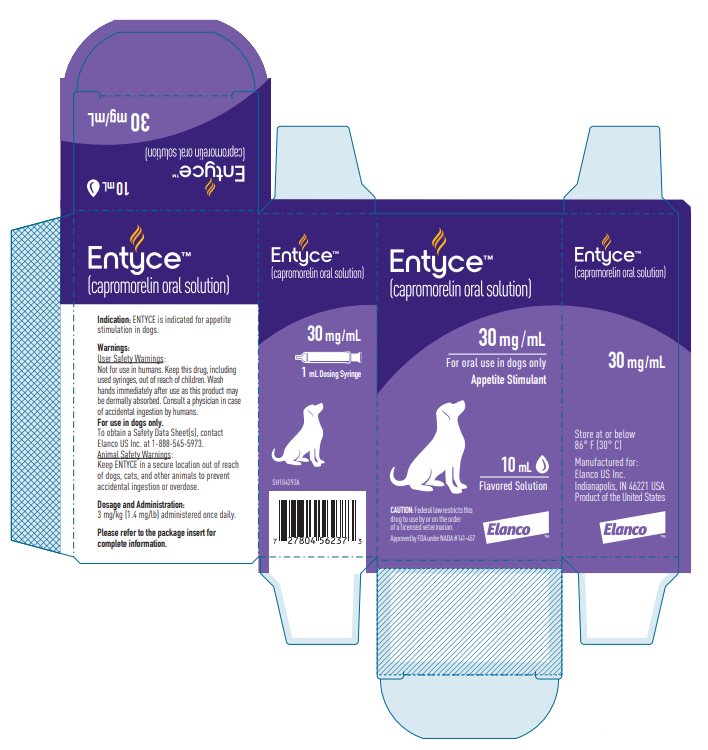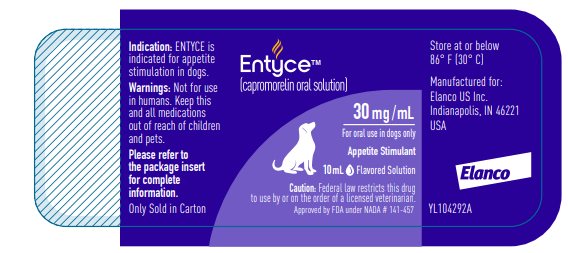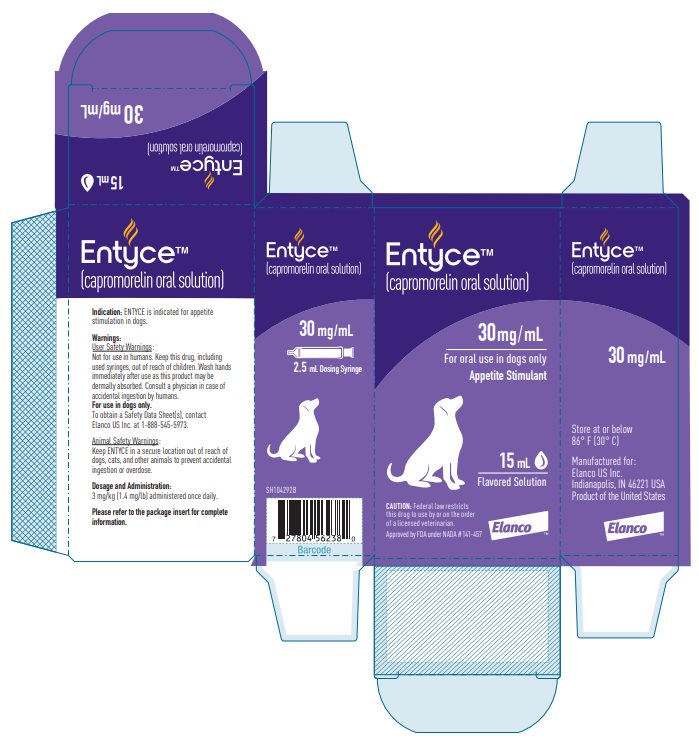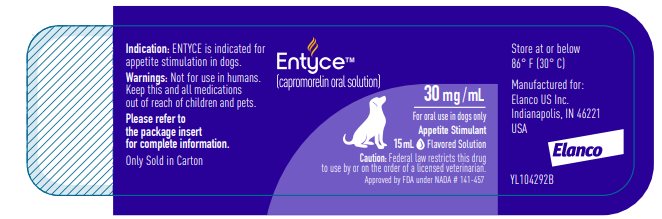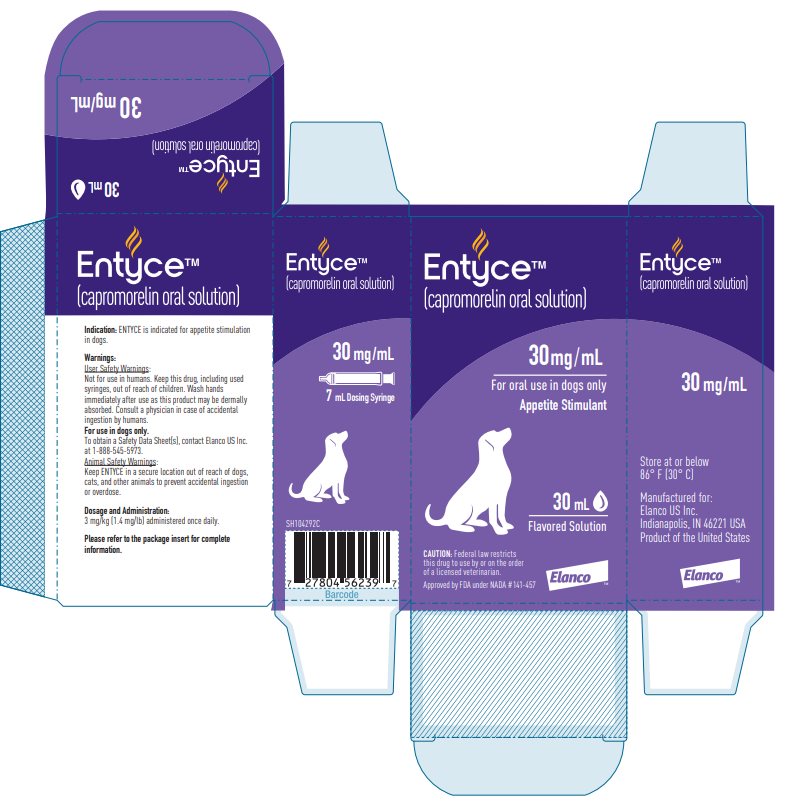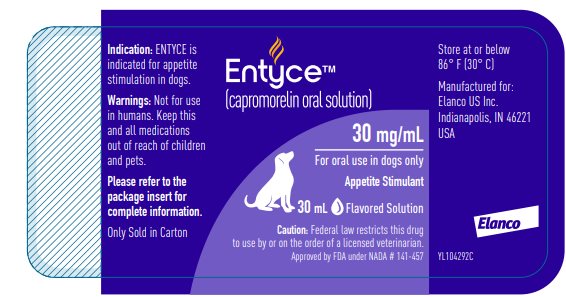 DRUG LABEL: Entyce
NDC: 58198-5535 | Form: SOLUTION
Manufacturer: Elanco US Inc.
Category: animal | Type: PRESCRIPTION ANIMAL DRUG LABEL
Date: 20251119

ACTIVE INGREDIENTS: Capromorelin tartrate 30 mg/1 mL

Entyce™

(capromorelin oral solution)

30 mg/mL

For oral use in dogs only

Appetite Stimulant

Caution:

Federal law restricts this drug to use by or on the order of a licensed veterinarian.

Description:

ENTYCE (capromorelin oral solution) is a selective ghrelin receptor agonist that binds to receptors and affects signaling in the hypothalamus to cause appetite stimulation and binds to the growth hormone secretagogue receptor in the pituitary gland to increase growth hormone secretion. The empirical formula is C28H35N5O4·C4H6O6 and the molecular weight 655.70. The chemical name is 2-amino-N-[2-(3aR-benzyl-2-methyl-3-oxo-2,3,3a,4,6,7-hexahydro-pyrazolo[4,3-c]pyridin-5-yl)1R-benzyloxymethyl-2-oxo-ethyl]-isobutyramide L-tartrate.

The chemical structure of capromorelin tartrate is:

Indication:

ENTYCE (capromorelin oral solution) is indicated for appetite stimulation in dogs.

Dosage and Administration:

Administer ENTYCE orally at a dose of 3 mg/kg (1.4 mg/lb) body weight once daily.

To administer ENTYCE follow the written instructions below and see illustrations 1 through 4 for administration steps.

1. Gently shake the bottle.
2. Remove the bottle cap and insert the provided dosing syringe firmly into the opening of the bottle.
3. Turn the bottle upside down and withdraw the appropriate volume of solution. Return the bottle to the upright position before removing the syringe, and replace the cap.
4. Administer the solution with the syringe into the dog's mouth.

Rinse the syringe and plunger with water between treatment doses. Leave the syringe and plunger apart to dry. Wash hands immediately after use.

The effectiveness of ENTYCE has not been evaluated beyond 4 days of treatment in the clinical field study (See Effectiveness).

Contraindications:

ENTYCE should not be used in dogs that have a hypersensitivity to capromorelin.

Warnings:

User Safety Warnings:

Not for use in humans. Keep this drug, including used syringes, out of reach of children. Wash hands immediately after use as this product may be dermally absorbed. Consult a physician in case of accidental ingestion by humans. To obtain a Safety Data Sheet(s), contact Elanco US Inc. at 1-888-545-5973.

For use in dogs only.

Animal Safety Warnings:

Keep ENTYCE in a secure location out of reach of dogs, cats, and other animals to prevent accidental ingestion or overdose.

Precautions:

Use with caution in dogs with hepatic dysfunction. ENTYCE is metabolized by CYP3A4 and CYP3A5 enzymes (See Clinical Pharmacology).

Use with caution in dogs with renal insufficiency. ENTYCE is excreted approximately 37% in urine and 62% in feces (See Adverse Reactions and Clinical Pharmacology).

Use with caution in dogs that may have cardiac disease or severe dehydration. ENTYCE can cause transient decreases in heart rate and blood pressure following dose administration. Some dogs may exhibit clinical signs of bradycardia or hypotension following administration of ENTYCE (See Post-Approval Experience).

Use with caution in dogs with diabetes mellitus as hyperglycemia has been reported following administration of ENTYCE (See Post-Approval Experience).

The safe use of ENTYCE has not been evaluated in dogs used for breeding or pregnant or lactating bitches.

Adverse Reactions:

In a controlled field study, 244 dogs were evaluated for safety when administered either ENTYCE or a vehicle control (solution minus capromorelin) at a dose of 3 mg/kg once daily for 4 days. Enrolled dogs had a reduced or absent appetite for a minimum of 2 days prior to day 0 and had various medical conditions: arthritis (40); gastrointestinal disease (24); allergy (22); dental disease (22); cardiovascular disease (16); renal disease (13); and others. Some dogs may have experienced more than one of the adverse reactions during the study.

The following adverse reactions were observed:

Table 1: Adverse Reactions reported in dogs administered ENTYCE oral solution compared to vehicle control
Adverse Reactions | ENTYCE (n = 171) n (%) | Vehicle Control (n = 73) n (%)
GASTROINTESTINAL
Diarrhea | 12 (7.0 %) | 5 (6.8 %)
Vomiting | 11 (6.4 %) | 4 (5.5 %)
Hypersalivation | 4 (2.3 %) | 0 (0.0 %)
Abdominal discomfort | 2 (1.2 %) | 0 (0.0 %)
Flatulence | 2 (1.2 %) | 0 (0.0 %)
Nausea | 2 (1.2 %) | 0 (0.0 %)
CLINICAL PATHOLOGY
Elevated blood urea nitrogen | 7 (4.1 %) | 2 (2.7 %)
Elevated phosphorus | 4 (2.3 %) | 1 (1.4 %)
Elevated creatinine | 1 (0.6 %) | 1 (1.4 %)
OTHER
Polydipsia | 7 (4.1 %) | 1 (1.4 %)
Lethargy/depression | 2 (1.2 %) | 0 (0.0 %)

The following adverse reactions were reported in < 1% of dogs administered ENTYCE: hyperactivity, increase fecal volume, increase gut sounds, and polyuria.

Post-Approval Experience (2025):

The following adverse events are based on post-approval adverse drug experience reporting for ENTYCE. Not all adverse events are reported to FDA/CVM. It is not always possible to reliably estimate the adverse event frequency or establish a causal relationship to product exposure using these data.

The following adverse events in dogs are categorized in order of decreasing reporting frequency by body system and in decreasing order of reporting frequency within each body system:

Gastrointestinal: vomiting, hypersalivation, diarrhea

General: lethargy, polydipsia, weakness, hyperglycemia, recumbency

Behavioral: Unusual behaviors (some of these behaviors were related to avoidance of medication), vocalization, hyperactivity

Neurological: ataxia, loss of consciousness, disorientation, sedation

Respiratory: panting, dyspnea

Cardiovascular: bradycardia, hypotension

Contact Information:

To report suspected adverse drug experiences, contact Elanco US Inc. at 1-888-545-5973.

For additional information about reporting adverse drug experiences for animal drugs, contact FDA at 1-888-FDA-VETS or http://www.fda.gov/reportanimalae

Clinical Pharmacology:

Following oral administration of ENTYCE at a dose of 3 mg/kg to 12 Beagle dogs, absorption of capromorelin was rapid with the maximum concentration (Cmax) reached within 0.83 hr (Tmax). After Cmax, the plasma concentrations declined mono-exponentially with a short terminal half-life (T½) of approximately 1.19 hrs. There were no gender differences in capromorelin pharmacokinetics. The exposure (Cmax and AUC) of capromorelin increased with dose, but the increases were not dose proportional following single and repeat once daily administrations of capromorelin. There was no drug accumulation following repeat oral administration.

Table 2. Plasma PK parameters following oral administration of 3 mg/kg of ENTYCE
Parameter | Mean | SD
Tmax (hr) | 0.83 | 0.58
Cmax (ng/mL) | 330 | 143
AUCt (ng*hr/mL) | 655 | 276
AUCinf (ng*hr/mL) | 695 | 262
T½ (hr) | 1.19 | 0.17

The mean absolute oral bioavailability of capromorelin was 44%. The mean total plasma clearance and volume of distribution was 18.9 mL/min/kg and 2.0 L/kg, respectively. Capromorelin was not highly bound (unbound fraction 51%) to plasma protein. The protein binding was concentration-independent over the range of 10 to 1000 ng/mL. In vitro (human liver microsomes) and in vivo (rats) metabolism studies suggest that capromorelin is metabolized by hepatic enzymes, mainly CYP3A4 and CYP3A5. Therefore, drugs that inhibit CYP3A4 and CYP3A5 activity may affect capromorelin metabolism. Following oral administration of radio-labelled capromorelin to dogs, capromorelin was excreted in urine (37%) and in feces (62%) within 72 hours.

Effectiveness:

Laboratory Effectiveness Study: Twenty four healthy Beagle dogs (6 dogs per sex in each group) with normal appetite were randomized into two groups and dosed daily with ENTYCE (capromorelin oral solution) at 3 mg/kg/day or vehicle control (solution minus capromorelin) to compare food intake over a 4-day period. The dogs were 13 months of age and weighed between 6.5 and 12.5 kg at the time of randomization. Six dogs administered ENTYCE repeatedly exhibited salivation post dosing and two dogs administered vehicle control exhibited salivation only one time on study day 0. Emesis was observed in one dog administered ENTYCE on study day 1. Dogs administered ENTYCE at a dose of 3 mg/kg/day for 4 consecutive days had statistically significantly increased food consumption compared to the vehicle control group (p < 0.001).

Clinical Field Study: Effectiveness was evaluated in 177 dogs (121 dogs in the ENTYCE group and 56 dogs in the vehicle control group) in a double-masked, vehicle controlled field study. Dogs with a reduced appetite or no appetite, with various medical conditions, for a minimum of 2 days prior to day 0 were enrolled in the study. The dogs ranged in age from 4 months to 18 years. Dogs were randomized to treatment group and dosed once daily for 4 days with ENTYCE at 3 mg/kg or vehicle control. Dogs were assessed for appetite by owners on day 0 and day 3 ± 1 using an “increased”, “no change” or “decreased” scoring system. Dogs were classified as a treatment success if the owner scored their dog's appetite as “increased” on day 3 ± 1. The success rates of the two groups were significantly different (p = 0.0078); 68.6% (n = 83) of dogs administered ENTYCE were successes, compared to 44.6% (n = 25) of the dogs in the vehicle control group.

Target Animal Safety:

In a 12-month laboratory safety study, 32 healthy Beagle dogs (4 dogs per sex per group) approximately 11-12 months of age and weighing 9-13.6 kg were dosed orally with capromorelin in deionized water daily at 0X (placebo), 0.3 (0.13X), 7 (3.07X), and 40 (17.5X) mg/kg/day. Administration of capromorelin was associated with increased salivation and reddening/swollen paws, increased liver weights and hepatocellular cytoplasmic vacuolation. Treatment related decreases were seen in red blood cell count, hemoglobin and hematocrit in the 40 mg/kg group. Pale skin, pale gums, and decreased red blood cell count, hemoglobin and hematocrit were observed in one dog administered 40 mg/kg/day. Increases were seen in cholesterol, high density lipoproteins, and the liver specific isozyme of serum alkaline phosphatase in the 40 mg/kg group. Growth hormone and insulin-like growth factor 1 plasma levels were increased in all groups administered capromorelin. There were no effects noted on gross necropsy. Capromorelin levels were similar in plasma collected on days 90, 181, and 349 indicating no accumulation of drug.

Storage Conditions:

Store at or below 86° F (30° C)

How Supplied:

30 mg/mL flavored solution in 10 mL, 15 mL and 30 mL bottles with measuring syringe

Approved by FDA under NADA # 141-457

Manufactured for:
Elanco US Inc.
Indianapolis, IN 46221 USA

Revised: August 2025

ENTYCE, Elanco and the diagonal bar logo are trademarks of Elanco or its affiliates.

© 2025 Elanco or its affiliates

ElancoTM
PA104292X

Principal Display Panel - 10 mL Carton Label

Entyce™

(capromorelin oral solution)

30 mg/mL

For oral use in dogs only

Appetite Stimulant

10 mL
Flavored Solution

Caution: Federal law restricts this
drug to use by or on the order
of a licensed veterinarian.

Approved by FDA under NADA #141-457

ElancoTM

Principal Display Panel - 10 mL Bottle Label

Entyce™

(capromorelin oral solution)

30 mg/mL

For oral use in dogs only

Appetite Stimulant

10 mL Flavored Solution

Caution: Federal law restricts this drug
to use by or on the order of a licensed veterinarian.

Approved by FDA under NADA #141-457

Principal Display Panel - 15 mL Carton Label

Entyce™

(capromorelin oral solution)

30 mg/mL

For oral use in dogs only

Appetite Stimulant

15 mL
Flavored Solution

Caution: Federal law restricts
this drug to use by or on the order
of a licensed veterinarian.

Approved by FDA under NADA #141-457

ElancoTM

Principal Display Panel - 15 mL Bottle Label

Entyce™

(capromorelin oral solution)

30 mg/mL

For oral use in dogs only

Appetite Stimulant

15 mL Flavored Solution

Caution: Federal law restricts this drug
to use by or on the order of a licensed veterinarian.

Approved by FDA under NADA #141-457

Principal Display Panel - 30 mL Carton Label

Entyce™

(capromorelin oral solution)

30 mg/mL

For oral use in dogs only

Appetite Stimulant

30 mL
Flavored Solution

Caution: Federal law restricts
this drug to use by or on the order
of a licensed veterinarian.

Approved by FDA under NADA #141-457

ElancoTM

Principal Display Panel - 30 mL Bottle Label

Entyce™

(capromorelin oral solution)

30 mg/mL

For oral use in dogs only

Appetite Stimulant

30 mL Flavored Solution

Caution: Federal law restricts this drug
to use by or on the order of a licensed veterinarian.

Approved by FDA under NADA #141-457